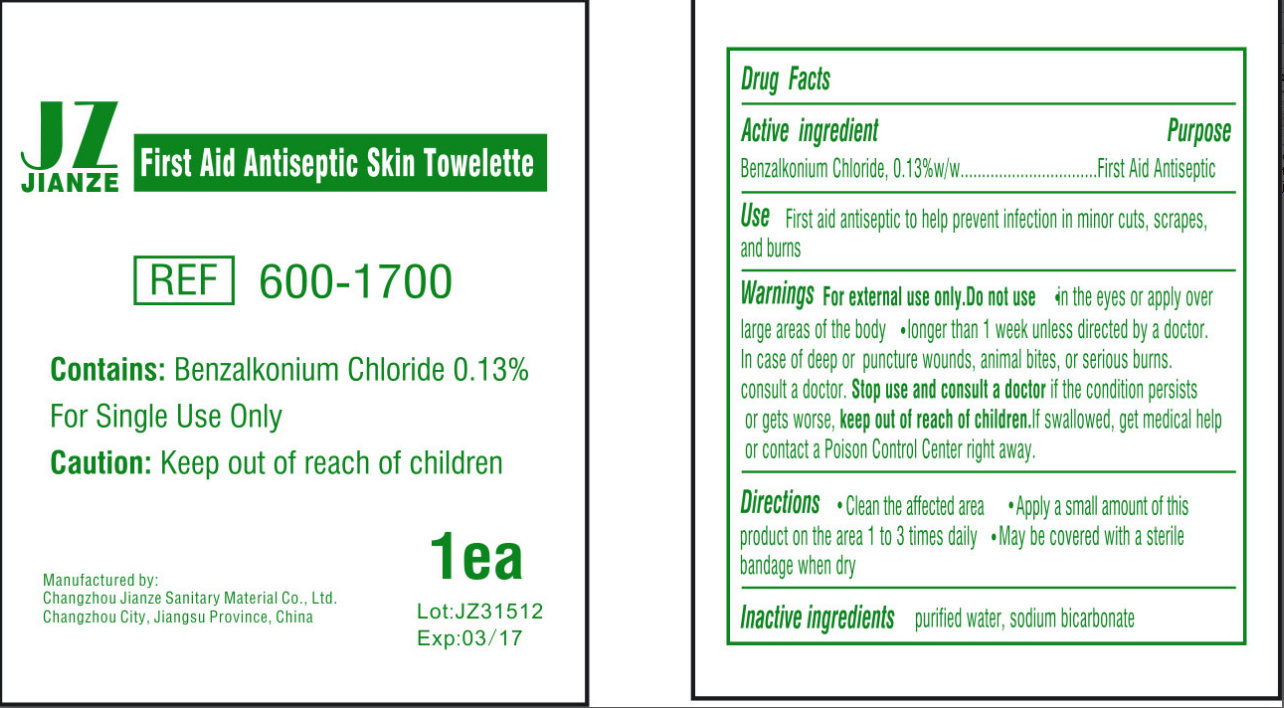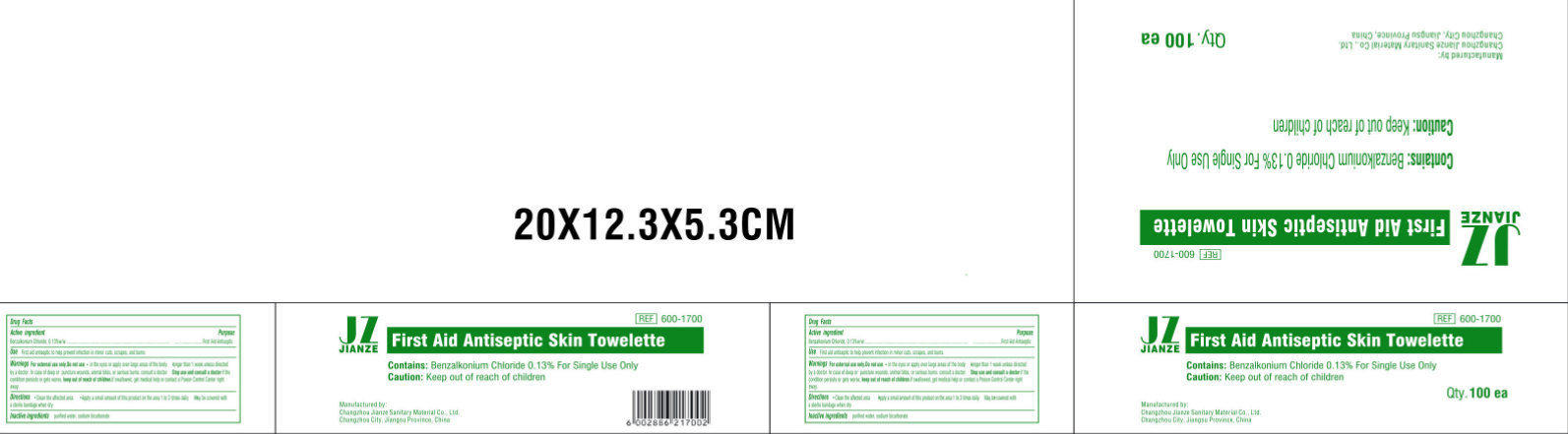 DRUG LABEL: JIANZE FIRST AID ANTISEPTIC SKIN TOWELETTE
NDC: 50666-007 | Form: LIQUID
Manufacturer: Changzhou Jianze Sanitary Material Co., Ltd.
Category: otc | Type: HUMAN OTC DRUG LABEL
Date: 20120620

ACTIVE INGREDIENTS: BENZALKONIUM CHLORIDE 0.13 g/100 g
INACTIVE INGREDIENTS: SODIUM BICARBONATE; WATER

JIANZE FIRST AID ANTISEPTIC SKIN TOWELETTE

ACTIVE INGREDIENT

Benzalkonium Chloride, 0.13%w/w

PURPOSE

First Aid Antiseptic

USE:

- First aid antiseptic to help prevent the risk of skin infection in minor cuts, scrapes, and burns.

WARNINGS:

For External Use Only
Do not use

- in the eyes or apply over large areas of the body
- longer than 1 week unless directed by a doctor.
- In case of deep or puncture wounds, animal bites, or serious burns Consult a doctor.

STOP USE AND CONSULT A DOCTOR

it the condition persists or gets worse.

KEEP OUT OF REACH OF CHILDREN.

In swallowed get medical help or contact a Poison Control Center right away.

DIRECTIONS

- Clean the affected area
- Apply a small amount of this product on the area 1 to 3 times daily
- May be covered with a sterile bandage when dry

INACTIVE INGREDIENTS:

Purified Water, Sodium Bicarbonate